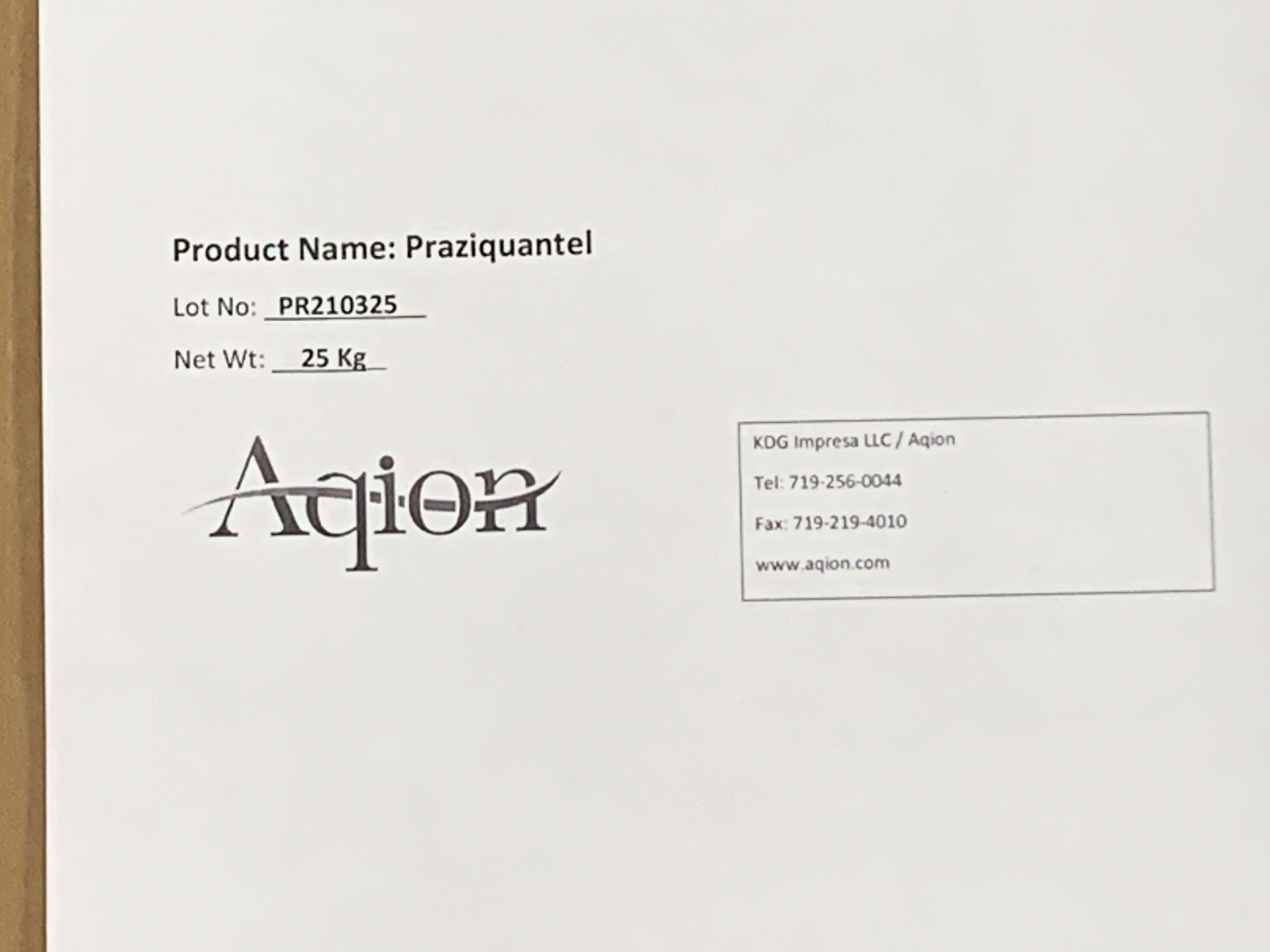 DRUG LABEL: Praziquantel
NDC: 43457-534 | Form: POWDER
Manufacturer: KDG Impresa LLC, Aqion
Category: other | Type: BULK INGREDIENT - ANIMAL DRUG
Date: 20250606

ACTIVE INGREDIENTS: PRAZIQUANTEL 1 kg/1 kg

Praziquantel